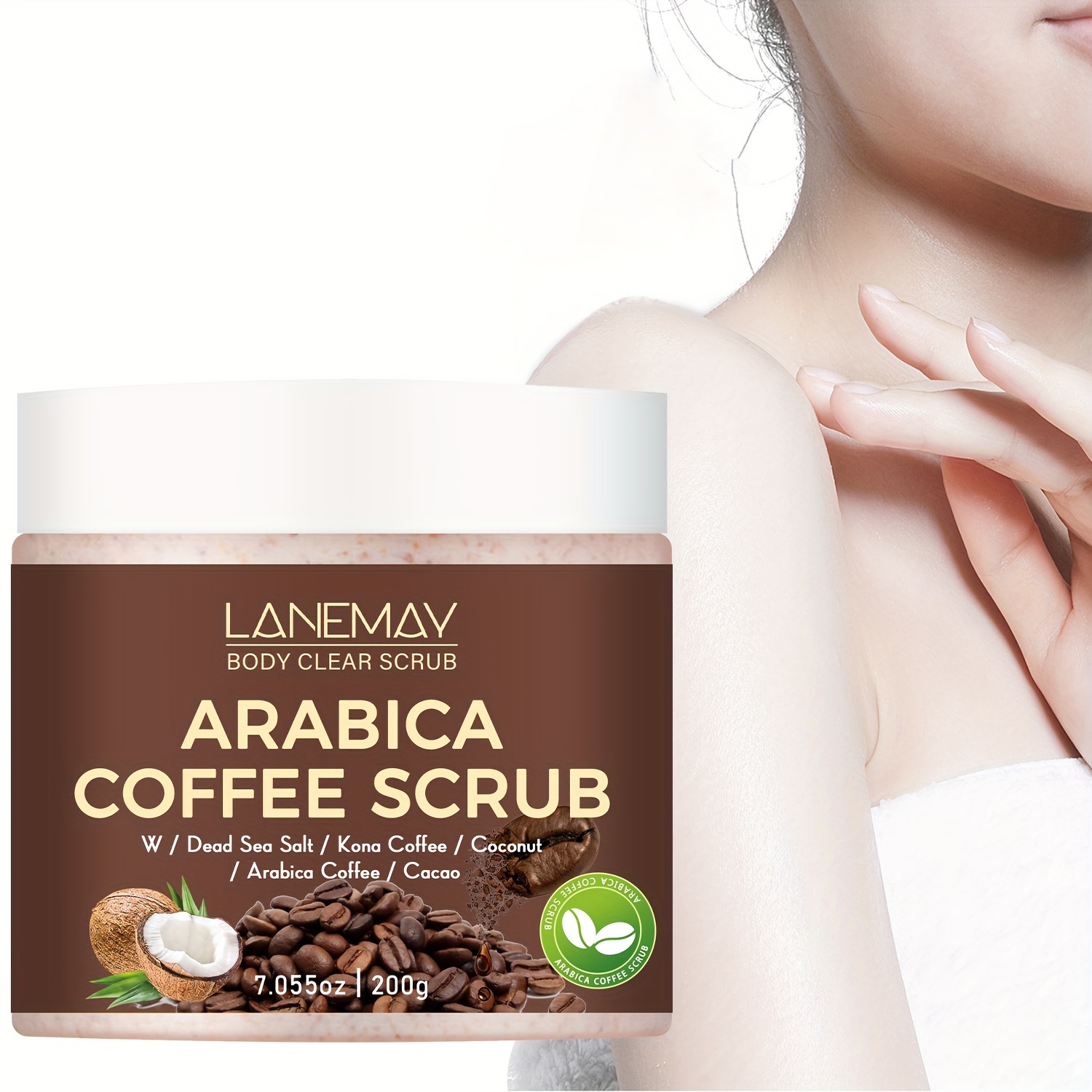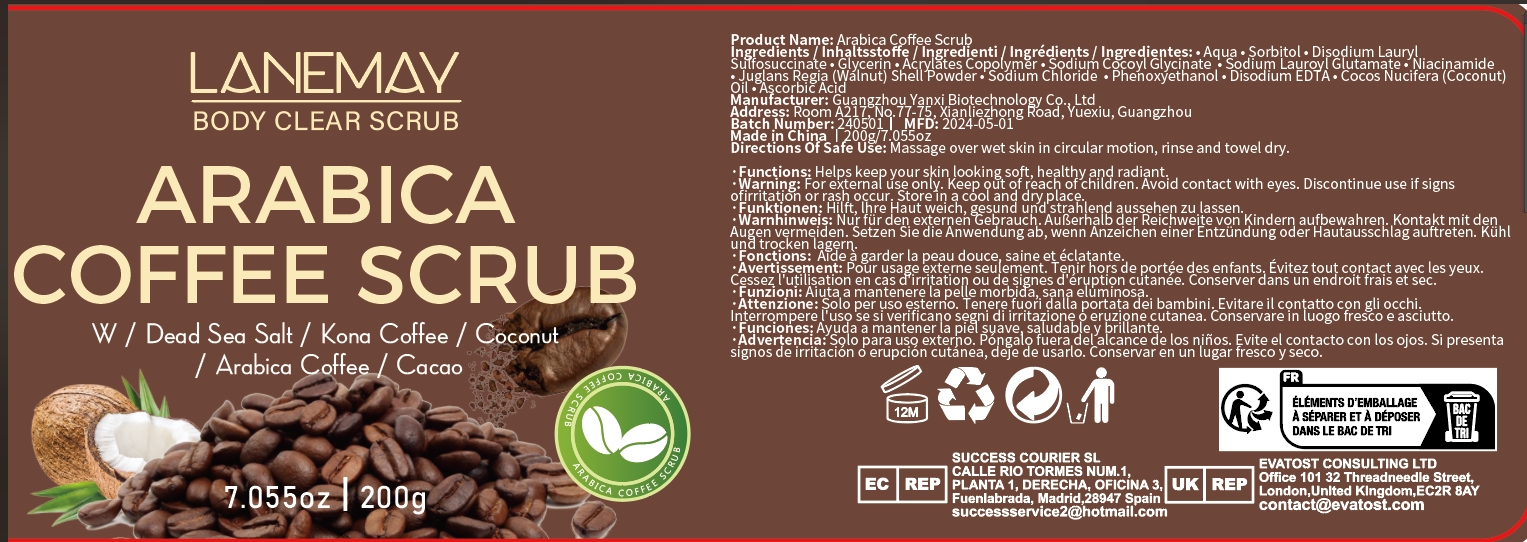 DRUG LABEL: Arabica Coffee Scrub
NDC: 84025-071 | Form: CREAM
Manufacturer: Guangzhou Yanxi Biotechnology Co., Ltd
Category: otc | Type: HUMAN OTC DRUG LABEL
Date: 20240720

ACTIVE INGREDIENTS: NIACINAMIDE 5 mg/100 mL; ASCORBIC ACID 3 mg/100 mL
INACTIVE INGREDIENTS: WATER

DOSAGE AND ADMINISTRATION

After using bath fluid, dig out a small amount of scrub cream for the palm, add some water to slowly blend, apply to the whole body

WARNINGS

keep out of children

INACTIVE INGREDIENT

Aqua

INDICATIONS AND USAGE

Body Horny thick

keep out of chlidren

PURPOSE

Gentle exfoliationImprove skin conditionMoisturize skin